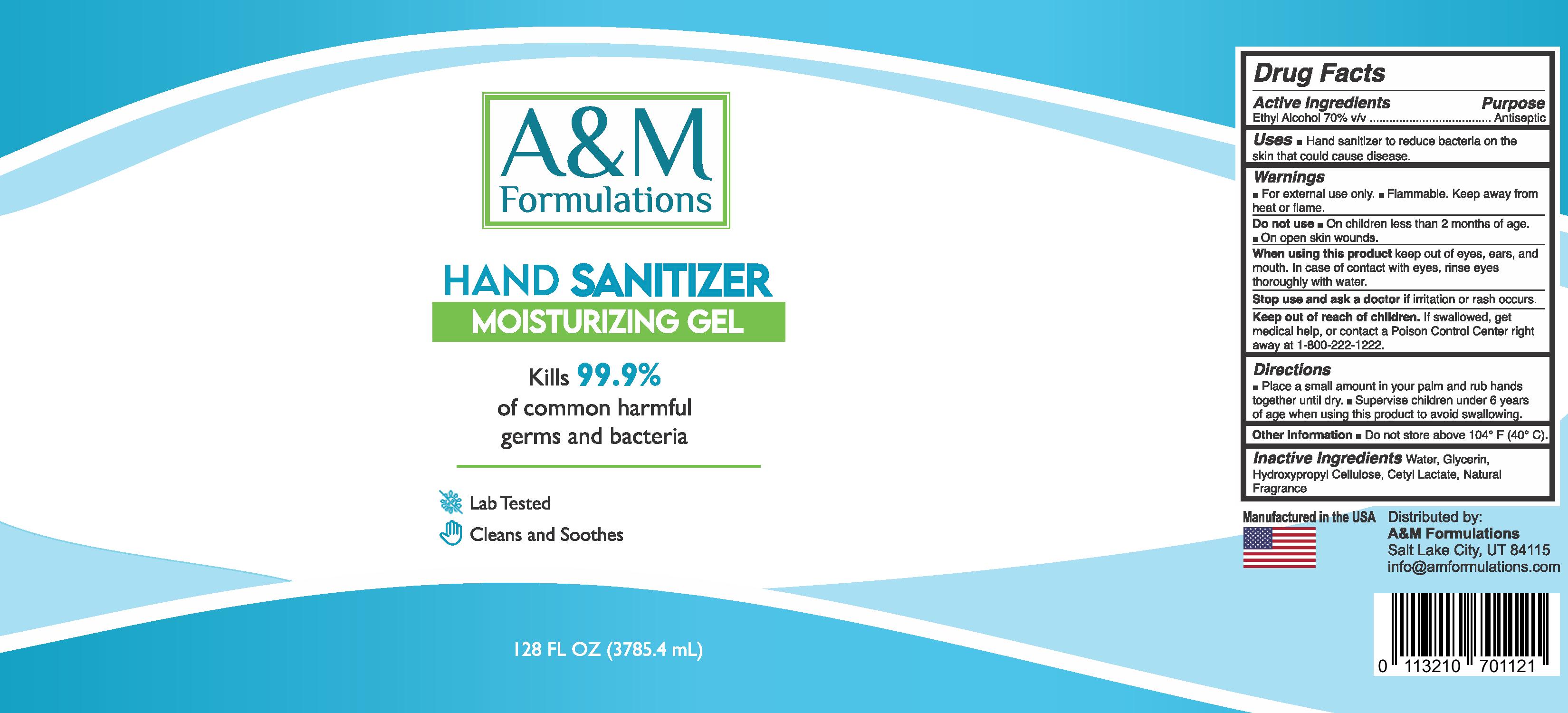 DRUG LABEL: Moisturizing Hand Sanitizer
NDC: 80375-001 | Form: GEL
Manufacturer: American Chemical LLC
Category: otc | Type: HUMAN OTC DRUG LABEL
Date: 20200921

ACTIVE INGREDIENTS: ALCOHOL 70 g/100 g
INACTIVE INGREDIENTS: WATER; LIMONENE, (+)-; GLYCERIN; HYDROXYPROPYL CELLULOSE, UNSPECIFIED; CETYL LACTATE

Moisturizing Hand Sanitizer

Active Ingredient(s)

Alcohol 70% w/w. Purpose: Antiseptic

Purpose

Antiseptic, Hand Sanitizer

Use

Hand Sanitizer to help reduce bacteria on the skin that could cause disease.

Warnings

For external use only. Flammable. Keep away from heat or flame.

Do not use

- On children less than 2 months of age
- On open skin wounds

When using this product keep out of eyes, ears, and mouth. In case of contact with eyes, rinse eyes thoroughly with water.
Stop use and ask a doctor if irritation or rash occurs.
Keep out of reach of children. If swallowed, get medical help or contact a Poison Control Center right away at 1-800-222-1222.

Stop use and ask a doctor if irritation or rash occurs.

Keep out of reach of children. If swallowed, get medical help or contact a Poison Control Center right away at 1-800-222-1222.

Directions

- Place a small amount in your palms and rub hands together until dry.
- Supervise children under 6 years of age when using this product to avoid swallowing.

Other information

- Do not store above 104° F (40° C)

Inactive ingredients

Water, Glycerin, Hydroxypropyl Cellulose, Cetyl Lactate, Natural Fragrance